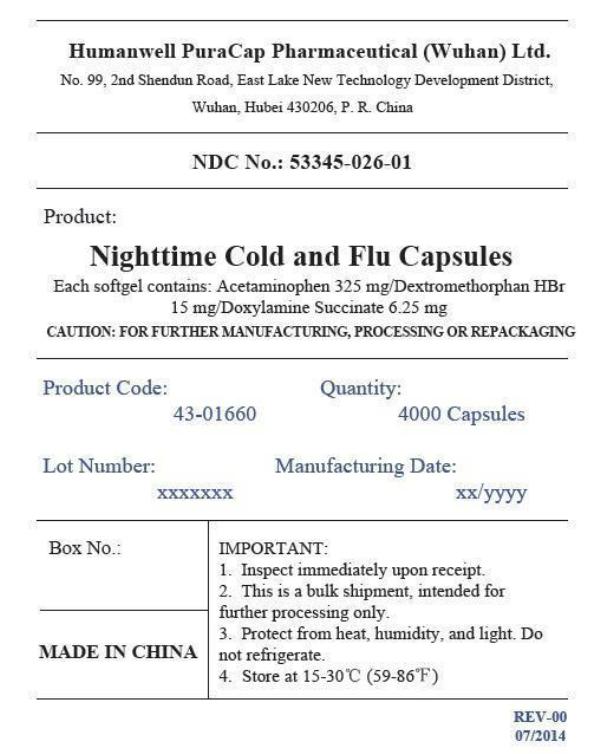 DRUG LABEL: Nighttime Cold and Flu
NDC: 53345-026 | Form: CAPSULE, LIQUID FILLED
Manufacturer: Humanwell PuraCap Pharmaceutical (Wuhan), Ltd.
Category: otc | Type: HUMAN OTC DRUG LABEL
Date: 20241125

ACTIVE INGREDIENTS: ACETAMINOPHEN 325 mg/1 1; DEXTROMETHORPHAN HYDROBROMIDE 15 mg/1 1; DOXYLAMINE SUCCINATE 6.25 mg/1 1
INACTIVE INGREDIENTS: D&C YELLOW NO. 10; FD&C BLUE NO. 1; GELATIN; GLYCERIN; POLYETHYLENE GLYCOL, UNSPECIFIED; POVIDONE; PROPYLENE GLYCOL; WATER; SORBITOL

NIGHTTIME COLD AND FLU capsule, liquid filled

Active ingredients (in each capsule)

Acetaminophen 325 mg

Dextromethorphan HBr 15 mg

Doxylamine Succinate 6.25 mg

Purpose

Pain reliever/ fever reducer

Cough suppressant

Antihistamine

Uses

temporarily relieves common cold/flu symptoms:

- cough due to minor throat & bronchial irritation
- sore throat
- headache
- minor aches/pains
- fever
- runny nose & sneezing

Warnings

Liver warningThis product contains acetaminophen. Severe liver damage may occur if you take:

- more than 4 doses in 24 hours, which is the maximum daily amount for this product
- with other drugs containing acetaminophen
- 3 or more alcoholic drinks daily while using this product

Sore throat warningIf sore throat is severe, lasts more than 2 days, occurs with or is followed by fever, headache, rash, nausea, or vomiting, see a doctor promptly.

Do not use

- with any other drug containing acetaminophen(prescription or nonprescription). If you are not sure whether a drug contains acetaminophen, ask a doctor or pharmacist.
- if you are now taking a prescription monoamine oxidase inhibitor (MAOI) (certain drugs for depression, psychiatric, or emotional conditions, or Parkinson's disease), or for 2 weeks after stopping the MAOI drug. If you do not know if your prescription drug contains an MAOI, ask a doctor or pharmacist before taking this product.
- To make a child sleep

Ask a doctor before use if you have

- liver disease
- glaucoma
- cough that occurs with too much phlegm (mucus)
- a breathing problem or chronic cough that lasts or as occurs with smoking, asthma, chronic bronchitis or emphysema
- trouble urinating due to enlarged prostate gland

Ask a doctor or pharmacist before use if you are

- taking sedatives or tranquilizers
- taking the blood thinning drug warfarin

When using this product

- do not use more than directed
- excitability may occur, especially in children
- marked drowsiness may occur
- avoid alcoholic drinks
- be careful when driving a motor vehicle or operating machinery
- alcohol, sedatives, and tranquilizers may increase drowsiness

Stop use and ask a doctor if

- pain or cough gets worse or lasts more than 7 days
- fever gets worse or lasts more than 3 days
- redness or swelling is present
- new symptoms occur
- cough comes back or occurs with rash or headache that lasts. These could be signs of a serious condition.

PREGNANCY OR BREAST FEEDING

If pregnant or breast-feeding,ask a health professional before use.

Keep out of reach of children.

Overdose warning

Taking more than directed can cause serious health problems. In case of overdose, get medical help or contact a Poison Control Center right away. Quick medical attention is critical for adults as well as children even if you do not notice any signs or symptoms.

Directions

- take only as directed - see Overdose warning
- do not exceed 4 doses per 24 hours

adults and children 12 years of age and over | take 2 softgels with water every 6 hours
children 4 to 12 years of age | ask a doctor
children under4 years o9f age | do not use

When using other Nighttime or Daytime products, carefully read each label to ensure correct dosing.

Other information

- store at room temperature 15°-30°C (59°-86°F)

Inactive ingredients

D&C Yellow # 10, FD&C Blue #1, gelatin, glycerin, polyethylene glycol, povidone, propylene glycol, purified water, sorbitol special, and white edible ink

Manufactured by:
Humanwell PuraCap Pharmaceutical (Wuhan) Ltd.
Wuhan, Hubei 430206,
China

PRINCIPAL DISPLAY PANEL - Shipping Label

NIGHTTIME COLD AND FLU CAPSULES

Quantity : 4000 Capsules
NDC. No : 53345-026-01

IMPORTANT:
1.Inspect immediately upon receipt.
2.This is a bulk shipment, intended for further processing only.
3.Protect from heat, humidity, and light. Do not refrigerate.
4.Store at 15-30°C (59-86°F)

CAUTION : "FOR FURTHER MANUFACTURING, PROCESSING OR REPACKAGING"